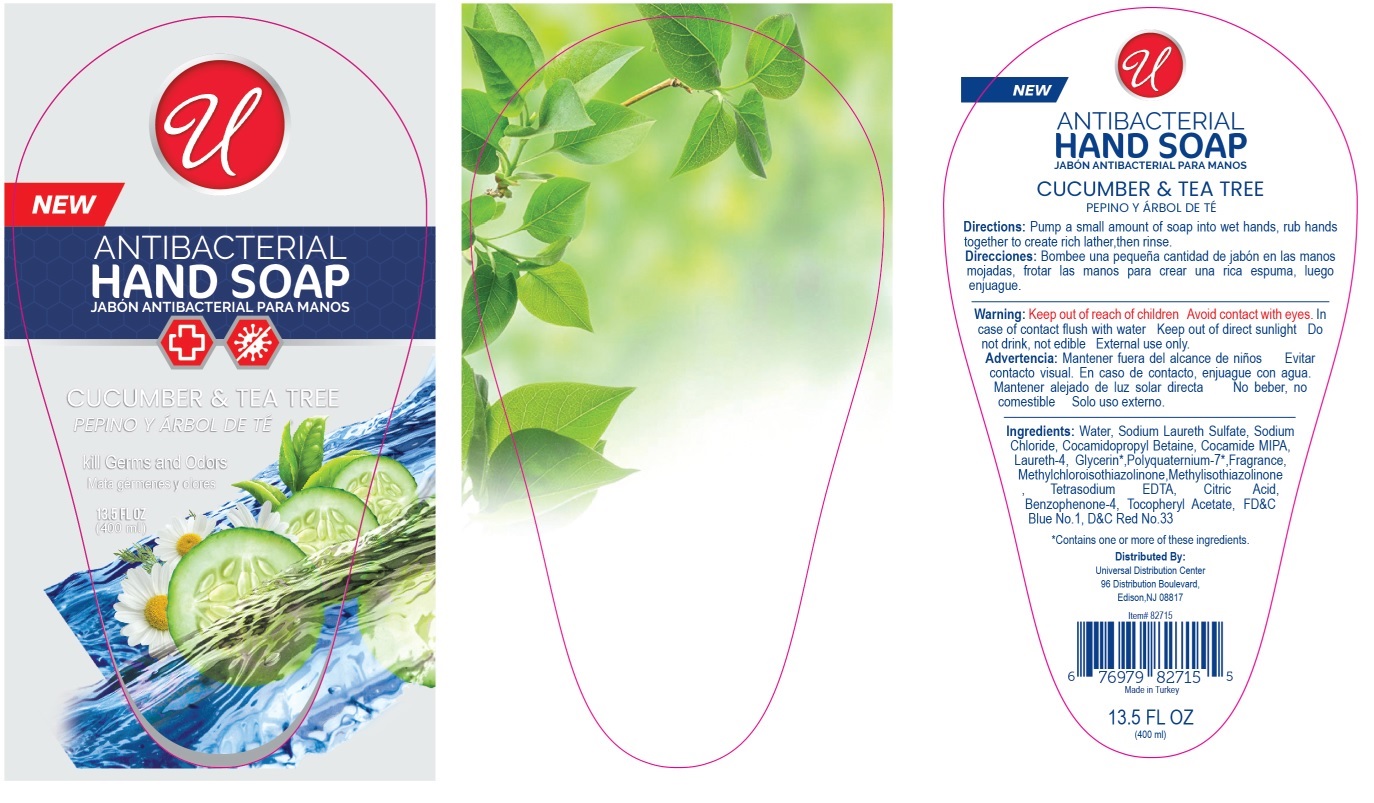 DRUG LABEL: ANTIBACTERIAL HANDWASH
NDC: 52000-048 | Form: LIQUID
Manufacturer: Universal Distribution Center LLC
Category: otc | Type: HUMAN OTC DRUG LABEL
Date: 20241206

ACTIVE INGREDIENTS: BENZALKONIUM CHLORIDE 0.13 g/100 mL
INACTIVE INGREDIENTS: WATER; SODIUM LAURETH-3 SULFATE; SODIUM CHLORIDE; COCAMIDOPROPYL BETAINE; COCO MONOISOPROPANOLAMIDE; LAURETH-4; GLYCERIN; POLYQUATERNIUM-7 (70/30 ACRYLAMIDE/DADMAC; 1600000 MW); METHYLCHLOROISOTHIAZOLINONE; METHYLISOTHIAZOLINONE; EDETATE SODIUM; CITRIC ACID MONOHYDRATE; SULISOBENZONE; .ALPHA.-TOCOPHEROL ACETATE; FD&C BLUE NO. 1; D&C RED NO. 33

ANTIBACTERIAL HANDWASH CUCUMBER & TEA TREE

Active ingredient

Benzalkonium Chloride 0.13%

Purpose

Antibacterial

INDICATIONS AND USAGE

USES for hand washing to decrease bacteria on the skin.

WARNINGS

Warning: Avoid contact with eyes. In case of contact flush with water. Keep out of direct sunlight. Do not drink, not edible. External use only.

Keep out of reach of children.

DOSAGE AND ADMINISTRATION

Directions: Pump a small amount of soap into wet hands, rub hands together to create rich lather, then rinse.

INACTIVE INGREDIENT

Ingredients: Water, Sodium Laureth Sulfate, Sodium Chloride, Cocamidopropyl Betaine, Cocamide MIPA, Laureth-4, Glycerin*, Polyquaternium-7*, Fragrance, Methylchloroisothiazolinone, Methylisothiazolinone, Tetrasodium EDTA, Citric Acid, Benzophenono-4, Tocopheryl Acetate, FD&C Blue No. 1, D&C Red No. 33

*Contains one or more of these ingredients.

Kill Germs and Odors

Distributed By:
Universal Distribution Center
96 Distribution Boulevard,
Edison, NJ 08817

Made in Turkey